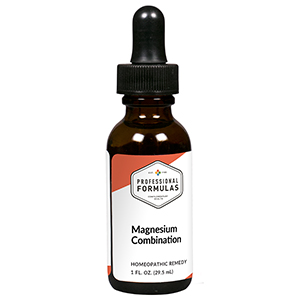 DRUG LABEL: Magnesium Combination
NDC: 63083-9232 | Form: LIQUID
Manufacturer: Professional Complementary Health Formulas
Category: homeopathic | Type: HUMAN OTC DRUG LABEL
Date: 20190815

ACTIVE INGREDIENTS: ARTEMISIA ANNUA FLOWERING TOP 3 [hp_X]/29.5 mL; PASSIFLORA INCARNATA FLOWERING TOP 3 [hp_X]/29.5 mL; AMANITA MUSCARIA FRUITING BODY 4 [hp_X]/29.5 mL; AMMONIUM BROMIDE 4 [hp_X]/29.5 mL; ACONITUM NAPELLUS WHOLE 6 [hp_X]/29.5 mL; ATROPINE SULFATE 6 [hp_X]/29.5 mL; CITRULLUS COLOCYNTHIS FRUIT PULP 6 [hp_X]/29.5 mL; CUPRIC CATION 6 [hp_X]/29.5 mL; GELSEMIUM SEMPERVIRENS ROOT 6 [hp_X]/29.5 mL; HYOSCYAMUS NIGER 6 [hp_X]/29.5 mL; MAGNESIUM PHOSPHATE, DIBASIC TRIHYDRATE 6 [hp_X]/29.5 mL; VERATRUM ALBUM ROOT 6 [hp_X]/29.5 mL
INACTIVE INGREDIENTS: ALCOHOL; WATER

R232

ACTIVE INGREDIENTS

Chamomilla 3X
Passiflora incarnata 3X
Agaricus muscarius 4X
Ammonium bromatum 4X
Aconitum napellus 6X
Atropinum sulphuricum 6X
Colocynthis 6X
Cuprum sulphuricum 6X
Gelsemium sempervirens 6X
Hyoscyamus niger 6X
Magnesia phosphorica 6X
Veratrum album 6X

QUESTIONS

Professional Formulas

PO Box 2034 Lake Oswego, OR 97035

INDICATIONS

For the temporary relief of muscular spasms, aches, or pain.*

PURPOSE

*Claims based on traditional homeopathic practice, not accepted medical evidence. Not FDA evaluated.

WARNINGS

In case of overdose, get medical help or contact a poison control center right away.

Keep out of the reach of children.

PREGNANCY OR BREAST FEEDING

If pregnant or breastfeeding, ask a healthcare professional before use.

DIRECTIONS

Place drops under tongue 30 minutes before/after meals. Adults and children 12 years and over: Take 10 drops up to 3 times per day. Consult a physician for use in children under 12 years of age.

OTHER INFORMATION

Tamper resistant. If seal is broken, do not use. After opening, close container tightly and store at room temperature away from heat.

INACTIVE INGREDIENTS

40% ethanol, purified water.

LABEL

Est 1985

Professional Formulas

Complementary Health

Magnesium Combination

Homeopathic Remedy

1 FL. OZ. (29.5 mL)